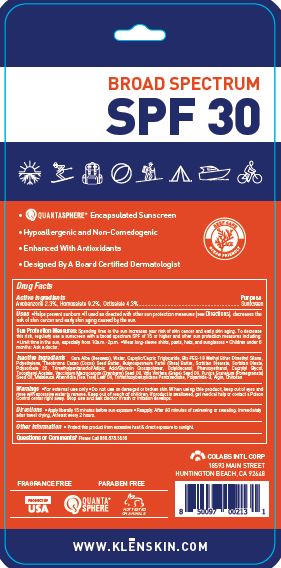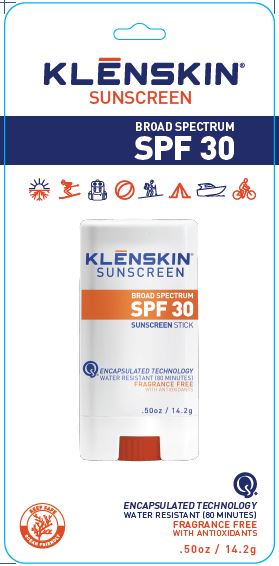 DRUG LABEL: KLENSKIN BROAD SPECTRUM SUNSCREEN
NDC: 61369-105 | Form: STICK
Manufacturer: CoLabs Intl. Corp
Category: otc | Type: HUMAN OTC DRUG LABEL
Date: 20240115

ACTIVE INGREDIENTS: AVOBENZONE 2.3 g/100 g; HOMOSALATE 9.2 g/100 g; OCTISALATE 4.3 g/100 g
INACTIVE INGREDIENTS: YELLOW WAX; WATER; MEDIUM-CHAIN TRIGLYCERIDES; BIS-PEG-18 METHYL ETHER DIMETHYL SILANE; HIGH DENSITY POLYETHYLENE; COCOA BUTTER; SHEA BUTTER; SORBITAN MONOSTEARATE; SORBITAN MONOOLEATE; POLYSORBATE 20; TRIMETHYLPENTANEDIOL/ADIPIC ACID/GLYCERIN CROSSPOLYMER (25000 MPA.S); OCTYLDODECANOL; PHENOXYETHANOL; CAPRYLYL GLYCOL; .ALPHA.-TOCOPHEROL ACETATE; CRANBERRY SEED OIL; GRAPE SEED OIL; POMEGRANATE SEED OIL; TEA TREE OIL; TRIMETHOXYBENZYLIDENE PENTANEDIONE; POLYAMIDE-3 (12000 MW); SODIUM ALGINATE; POLIGLUSAM

COLABS - KLENSKIN SUNSCREEN BROAD SPECTRUM SPF30 (61369-105)

ACTIVE INGREDIENTS

AVOBENZONE 2.3%

HOMOSALATE 9.2%

OCTISALATE 4.3%

PURPOSE

SUNSCREEN

USES

- HELPS PREVENT SUNBURN
- IF USED AS DIRECTED WITH OTHER SUN PROTECTION MEASURES (SEE DIRECTIONS), DECREASES THE RISK OF SKIN CANCER AND EARLY SKIN AGING CAUSED BY THE SUN.

WARNINGS

- FOR EXTERNAL USE ONLY
- DO NOT USE ON DAMAGED OR BROKEN SKIN.
- WHEN USING THIS PRODUCT, KEEP OUT OF EYES AND RINSE WITH EXCESSIVE WATER TO REMOVE.

KEEP OUT OF REACH OF CHILDREN. IF PRODUCT IS SWALLOWED, GET MEDICAL HELP OR CONTACT A POISON CONTROL CENTER RIGHT AWAY.

STOP USE AND ASK A DOCTOR IF RASH OR IRRITATION DEVELOPS.

DIRECTIONS

- APPLY LIBERALLY 15 MINUTES BEFORE SUN EXPOSURE
- REAPPLY:
- AFTER 80 MINUTES OF SWIMMING, SWEATING OR EXPOSURE TO WATER
- IMMEDIATELY AFTER TOWEL DRYING, AT LEAST EVERY 2 HOURS

OTHER SAFETY INFORMATION

SUN PROTECTION MEASURES: SPENDING TIME IN THE SUN INCREASES YOUR RISK OF SKIN CANCER AND EARLY SKIN AGING. TO DECREASE THIS RISK, REGULARLY USE A SUNSCREEN WITH A BROAD SPECTRUM SPF OF 15 OR HIGHER AND OTHER SUN PROTECTION MEASURES INCLUDING:

- LIMIT TIME IN THE SUN, ESPECIALLY FROM 10 A.M. - 2 P.M.
- WEAR LONG-SLEEVED SHIRTS, PANTS, HATS, AND SUNGLASSES
- CHILDREN UNDER 6 MONTHS: ASK A DOCTOR.

OTHER INFORMATION

- PROTECT THE PRODUCT IN THIS CONTAINER FROM EXCESSIVE HEAT AND DIRECT EXPOSURE TO SUNLIGHT.

INACTIVE INGREDIENTS

CERA ALBA (BEESWAX), WATER, CAPRYLIC/CAPRIC TRIGLYCERIDE, BIS-PEG-METHYL ETHER DIMETHYL SILANE, POLYETHYLENE, THEOBROMA CACAO (COCOA) SEED BUTTER, BUTYROSPERMUM PARKII (SHEA) BUTTER, SORBITAN STEARATE, SORBITAN OLEATE, POLYSORBATE 20, TRIMETHYLPENTANEDIOL/ADIPIC ACID/GLYCERIN CROSSPOLYMER, OCTYLDECANOL, PHENOXYETHANOL, CAPRYLYL GLYCOL, TOCOPHERYL ACETATE, VACCINIUM MACROCARPON (CRANBERRY) SEED OIL, VITIS VINIFERA (GRAPE) SEED OIL, PUNICA GRANATUM (POMEGRANATE) SEED OIL, MELALEUCA ALTERNIFOLIA (TEA TREE) LEAF OIL, TRIMETHOXYBENZYLIDENE PENTANEDIONE, POLYAMIDE-3, ALGIN, CHITOSAN

QUESTIONS OR COMMENTS?

PLEASE CALL TOLL FREE 888.878.5536